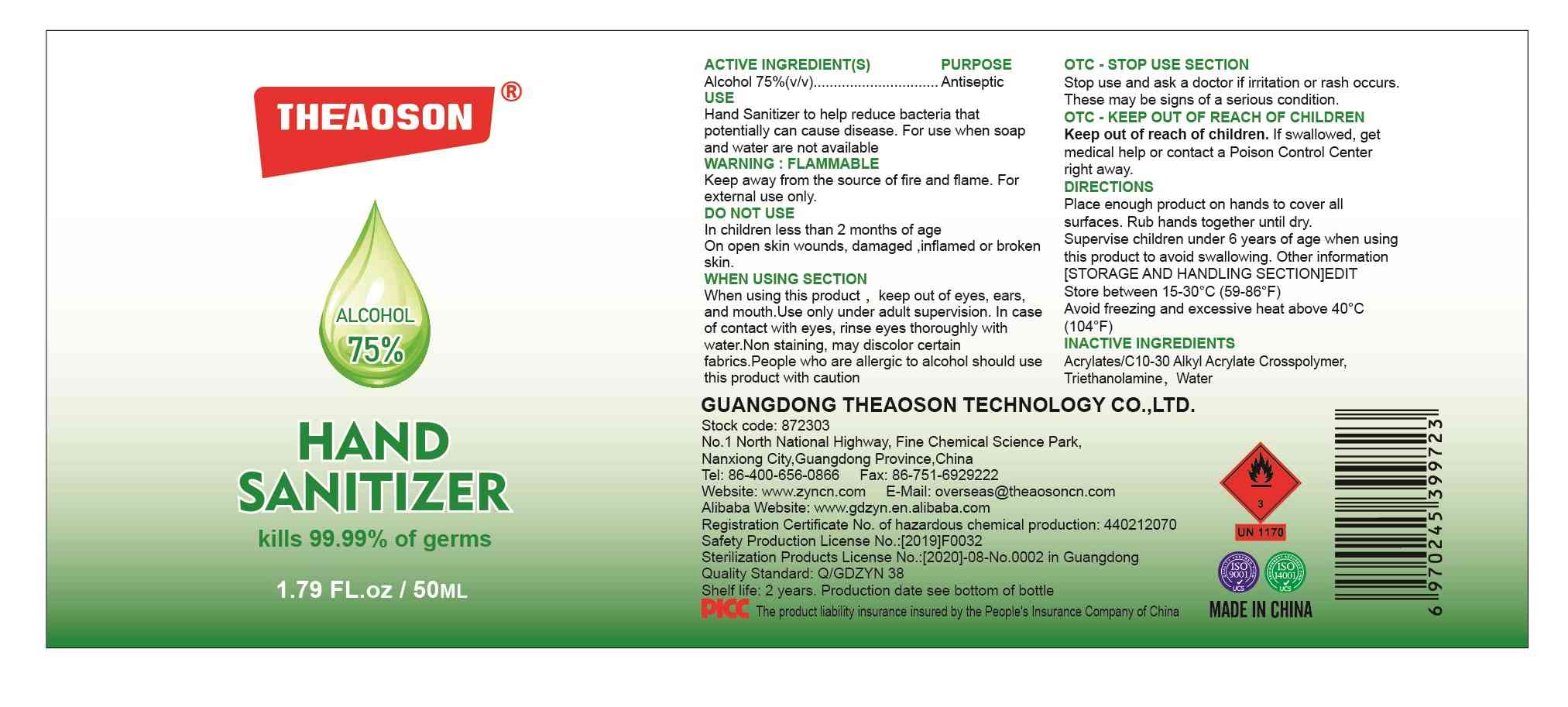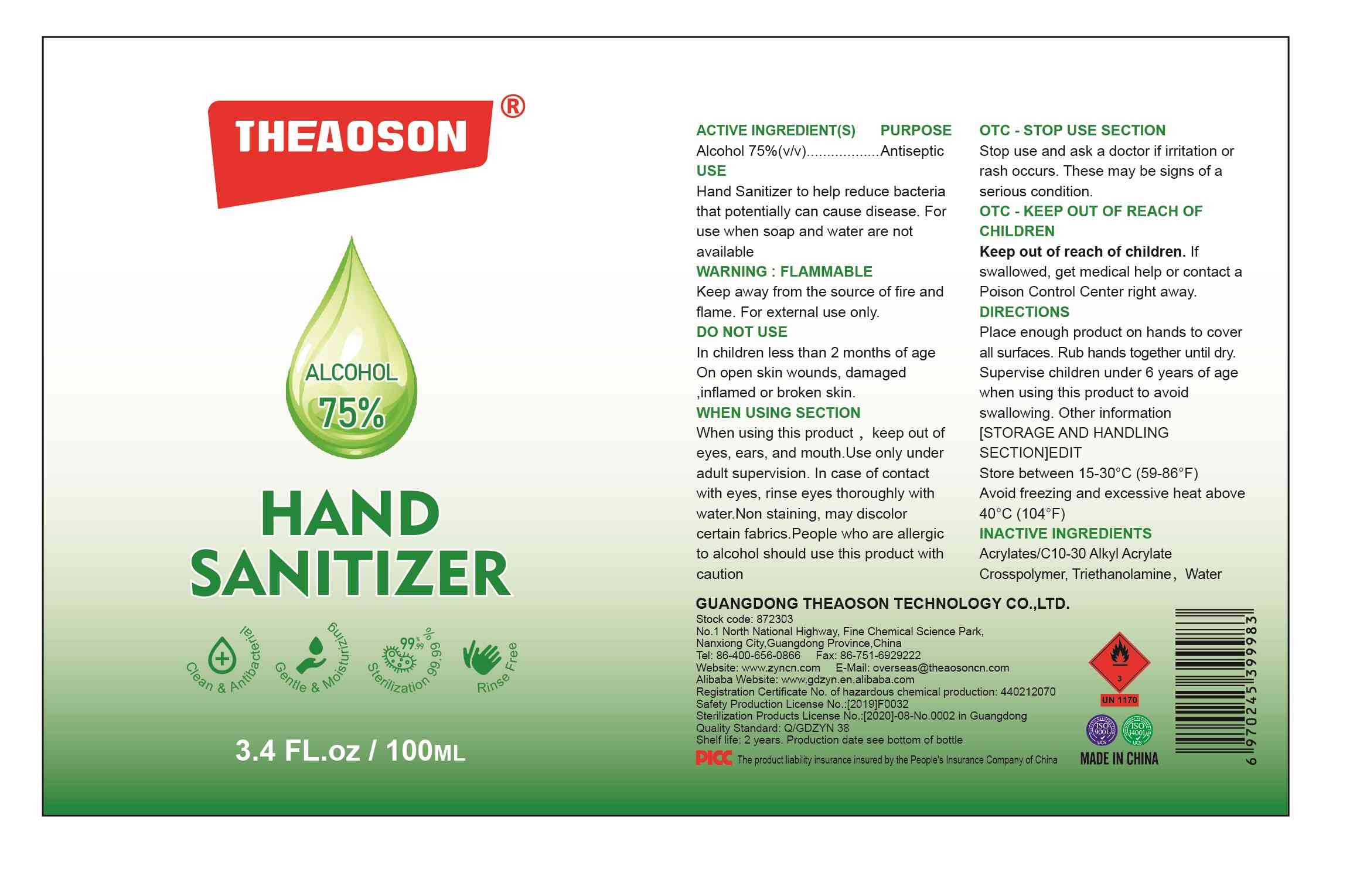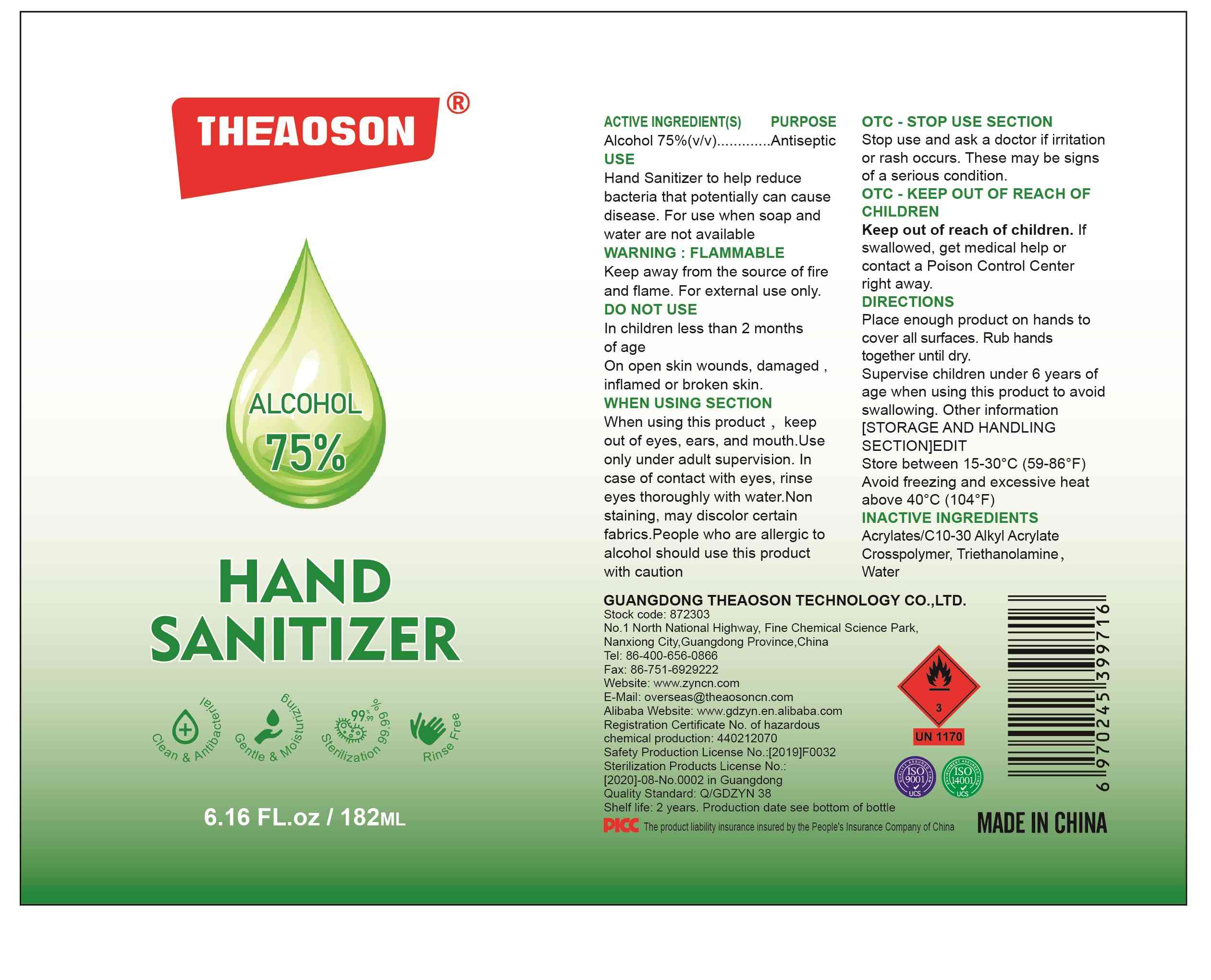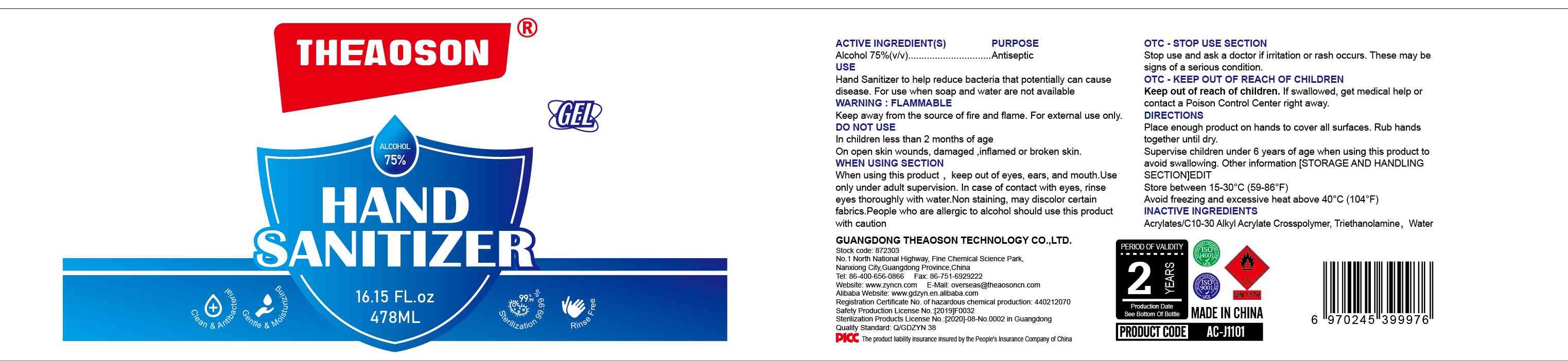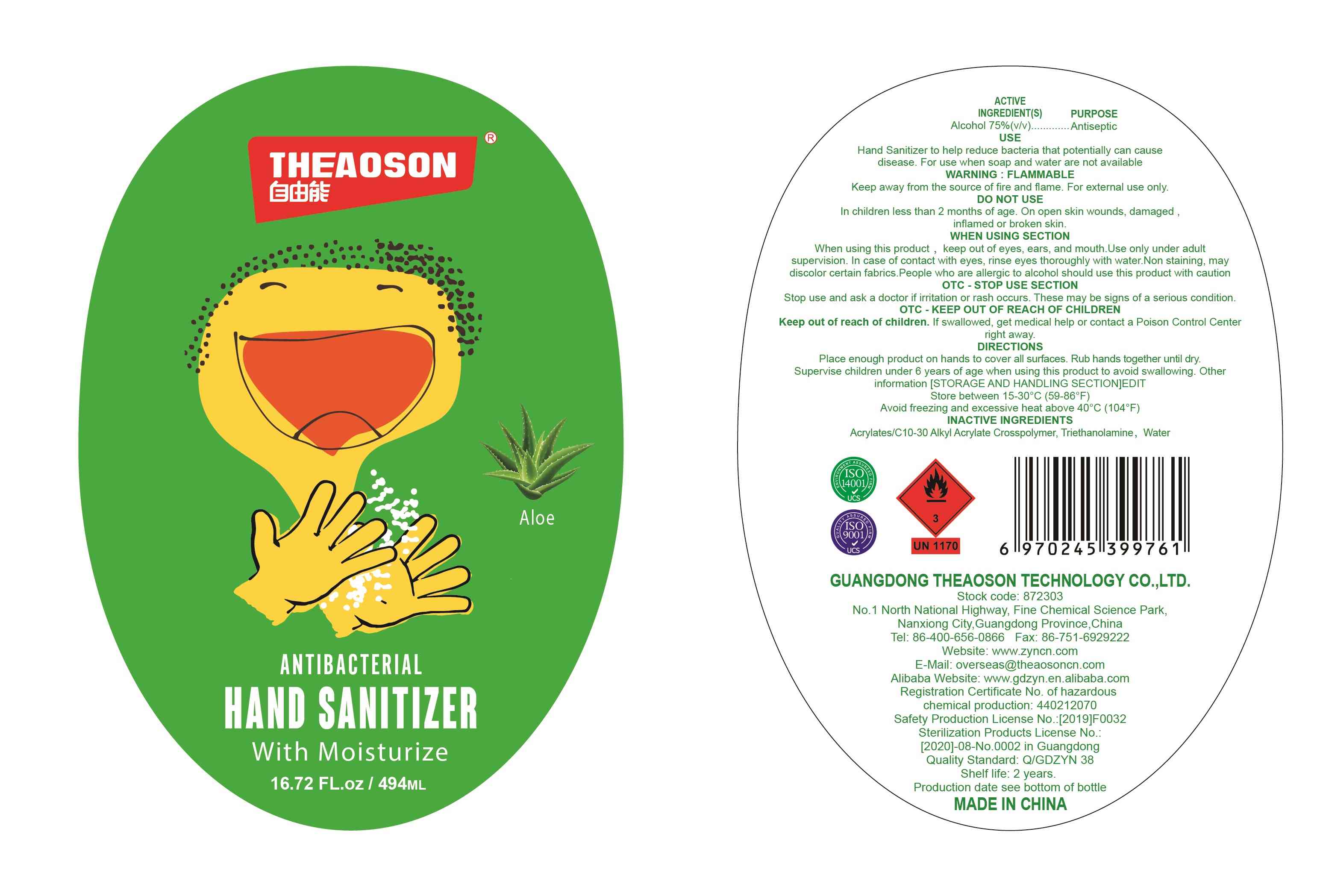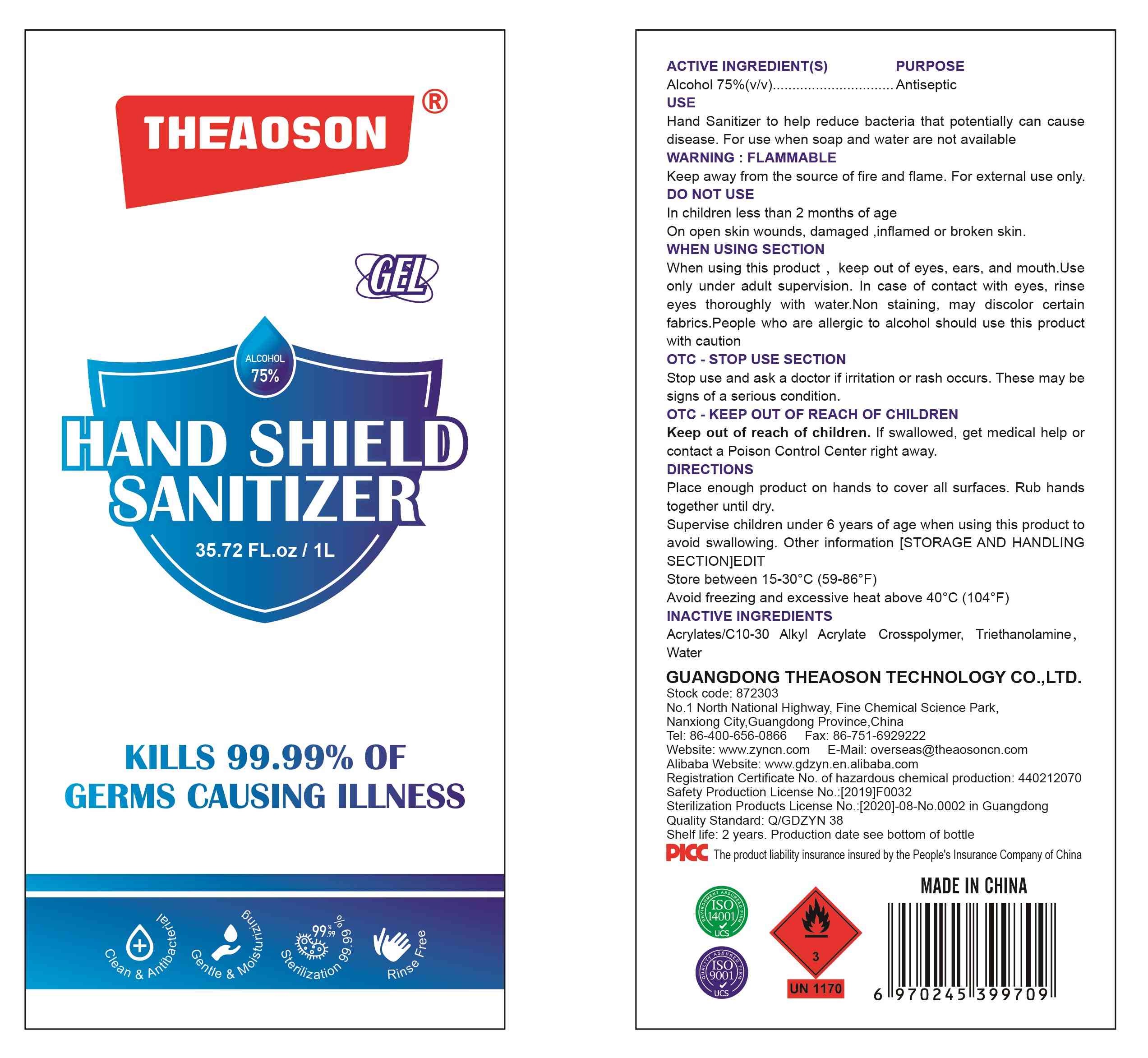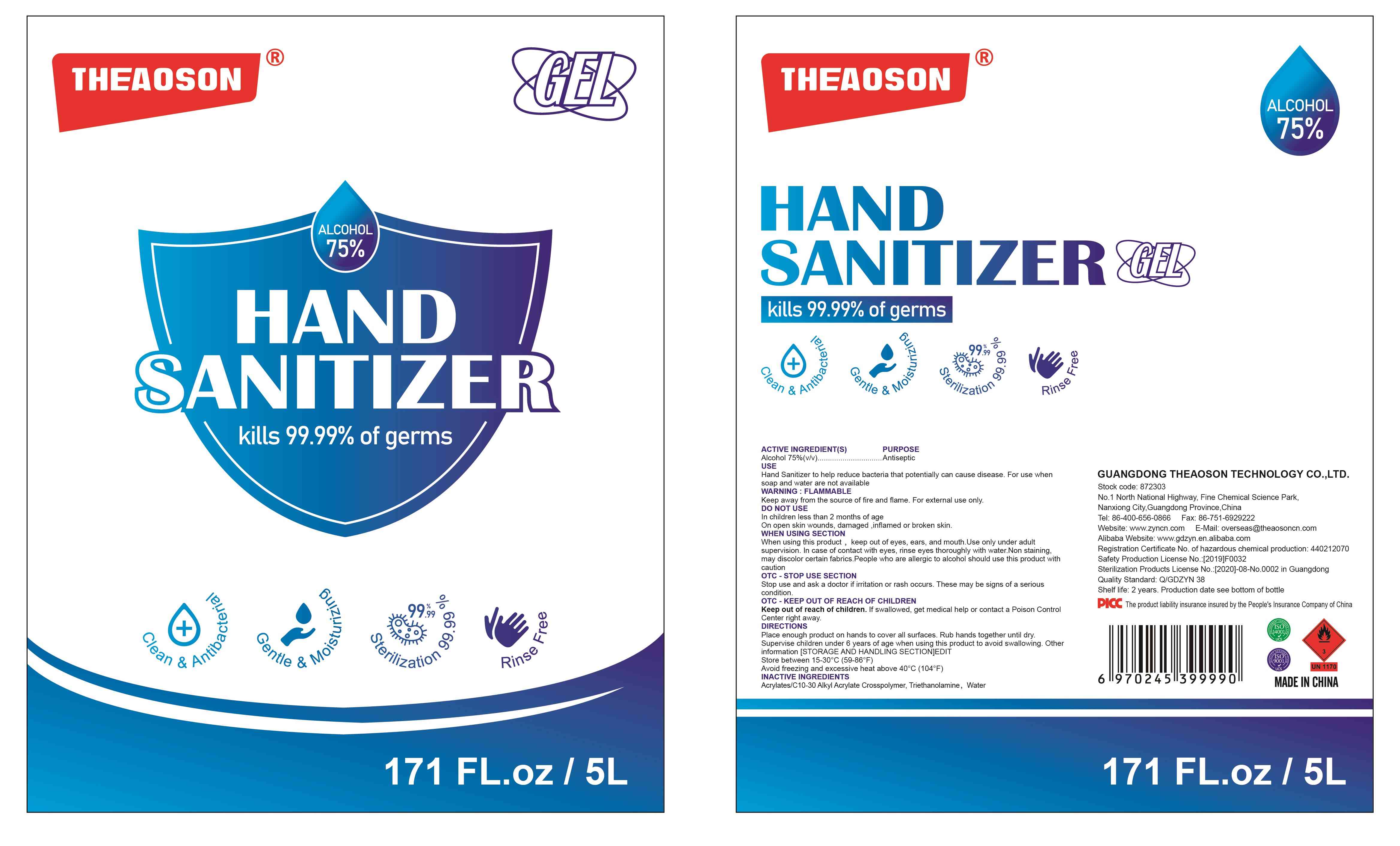 DRUG LABEL: ALCOHOL HAND SANITIZER
NDC: 78792-012 | Form: GEL
Manufacturer: GUANGDONG THEAOSON TECHNOLOGY CO.,LTD
Category: otc | Type: HUMAN OTC DRUG LABEL
Date: 20201215

ACTIVE INGREDIENTS: ALCOHOL 75 mL/100 mL
INACTIVE INGREDIENTS: TROLAMINE; WATER; CARBOMER INTERPOLYMER TYPE A (55000 CPS)

78792-012
ALCOHOL HAND SANITIZER

Active Ingredient(s)

Alcohol 75% v/v. Purpose: Antiseptic

Purpose

Antiseptic, Hand Sanitizer

Use

Hand Sanitizer to help reduce bacteria that potentially can cause disease. For use when soap and water are not available.

Warnings

Keep away from the source of fire and flame. For external use only.

Do not use

in children less than 2 months of age
on open skin wounds, damaged, inflamed or broken skin.

When using this product, keep out of eyes, ears, and mouth. Use only under adult supervision. In case of contact with eyes, rinse eyes thoroughly with water.
Non staining, may discolor certain fabrics. People who are allergic to alchohol shuld use this product with caution.
Stop use and ask a doctor if irritation or rash occurs. These may be signs of a serious condition.
Keep out of reach of children. If swallowed, get medical help or contact a Poison Control Center right away.

Stop use and ask a doctor if irritation or rash occurs. These may be signs of a serious condition.

Keep out of reach of children. If swallowed, get medical help or contact a Poison Control Center right away.

Directions

- Place enough product on hands to cover all surfaces. Rub hands together until dry.
- Supervise children under 6 years of age when using this product to avoid swallowing.

Other information

- Store between 15-30C (59-86F)
- Avoid freezing and excessive heat above 40C (104F)

Inactive ingredients

acrylates/ C10-30 Alkyl Acrylate Crosspolymer, Triethanolamine, water

Package Label - Principal Display Panel

78792-012-01 50ML

78792-012-02 100ML

78792-012-03 182ML

78792-012-04 478ML

78792-012-05 494ML

78792-012-06 1000ML

78792-012-07 5000ML